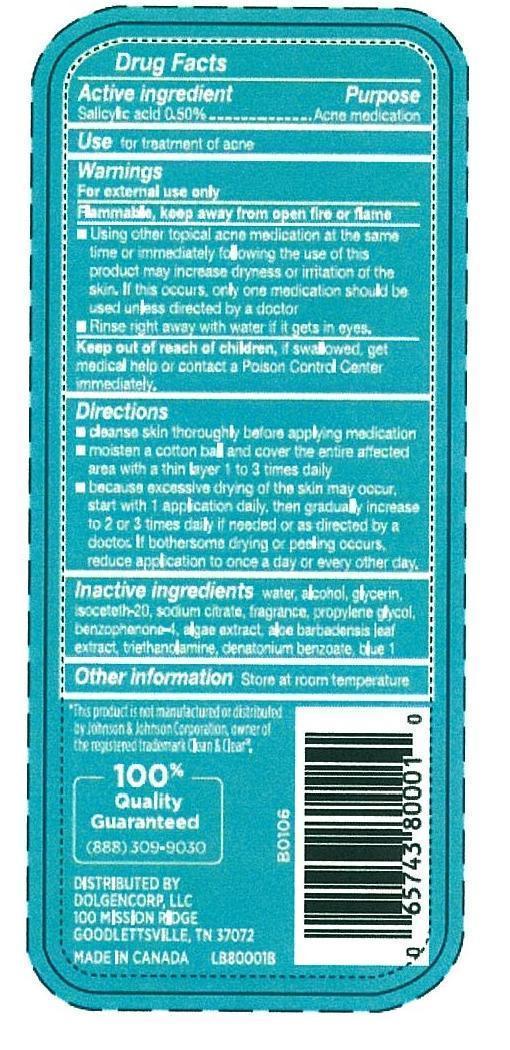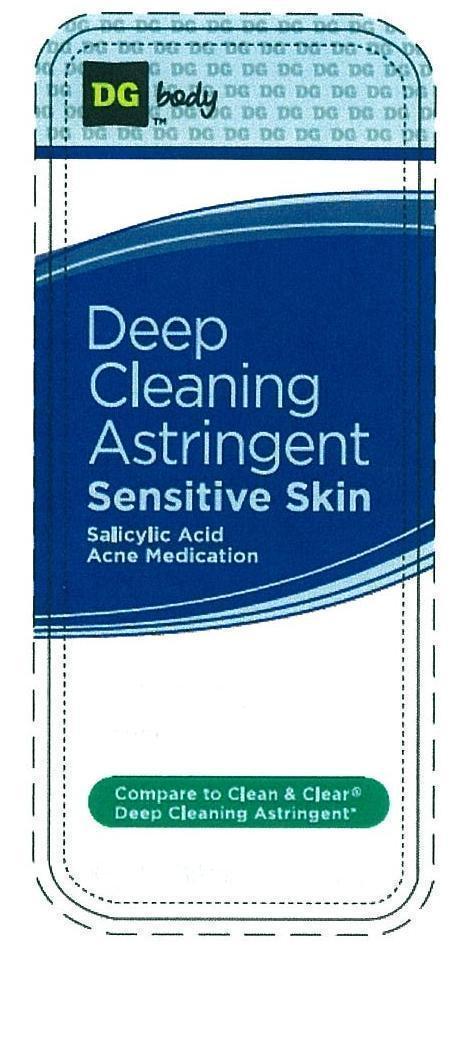 DRUG LABEL: DG Deep Cleaning Astringent Sensitive Skin
NDC: 60742-002 | Form: LIQUID
Manufacturer: BELVEDERE INTERNATIONAL INC.
Category: otc | Type: HUMAN OTC DRUG LABEL
Date: 20121207

ACTIVE INGREDIENTS: SALICYLIC ACID 0.5 g/100 g
INACTIVE INGREDIENTS: WATER; ALCOHOL; GLYCERIN; ISOCETETH-20; SODIUM CITRATE; TROLAMINE; PROPYLENE GLYCOL; BENZOPHENONE; ALOE; DENATONIUM BENZOATE; FD&C BLUE NO. 1

DRUG FACTS

DRUG FACTS

Active Ingredient

Salicylic acid 0.50%

PURPOSE

USE for treatment of acne

Keep out of reach of children, if swallowed, get medical help or contact a Poison Control Center immediately.

INDICATIONS AND USAGE

USE FOR TREATMENT OF ACNE

WARNINGS

FOR EXTERNAL USE ONLY, Flammable, keep awat from open fire or flame, Using other topical acne medication at the same time or immediately following the use fo this product may increase dryness or irritation of the skin. If this occurs, only one medication should be used unless directed by a doctor. Rinse right away with water if it gets in eyes.

DOSAGE AND ADMINISTRATION

- CLEANSE SKIN THOROUGHLY BEFORE APPLYING MEDICATION
- MOISTEN A COTTON BALL AND COVER THE ENTIRE AFFECTED AREA WITH A THIN LAYER 1 TO 3 TIMES DAILY
- BECAUSE EXCESSIVE DRYING OF THE SKIN MAY OCCUR, START WITH 1 APPLICATION DAILY. THEN GRADUALLY INCREASE TO 2 OR 3 TIMES DAILY IF NEEDED OR AS DIRECTED BY A DOCOR. IF BOTHERSOME DRYING OR PEELING OCCURS, REDUCE APPLICATION TO ONCE A DAY OR EVERY OTHER DAY.

INACTIVE INGREDIENT

WATER, Alcohol, Glycerin, Isoceteth-20, Sodium Citrate, Fragrance, Propylene Glycol, Benzophenone-4, Algae extract, Aloe barbadensis leaf extract, triethanolamine, denatonium benzoate, blue 1